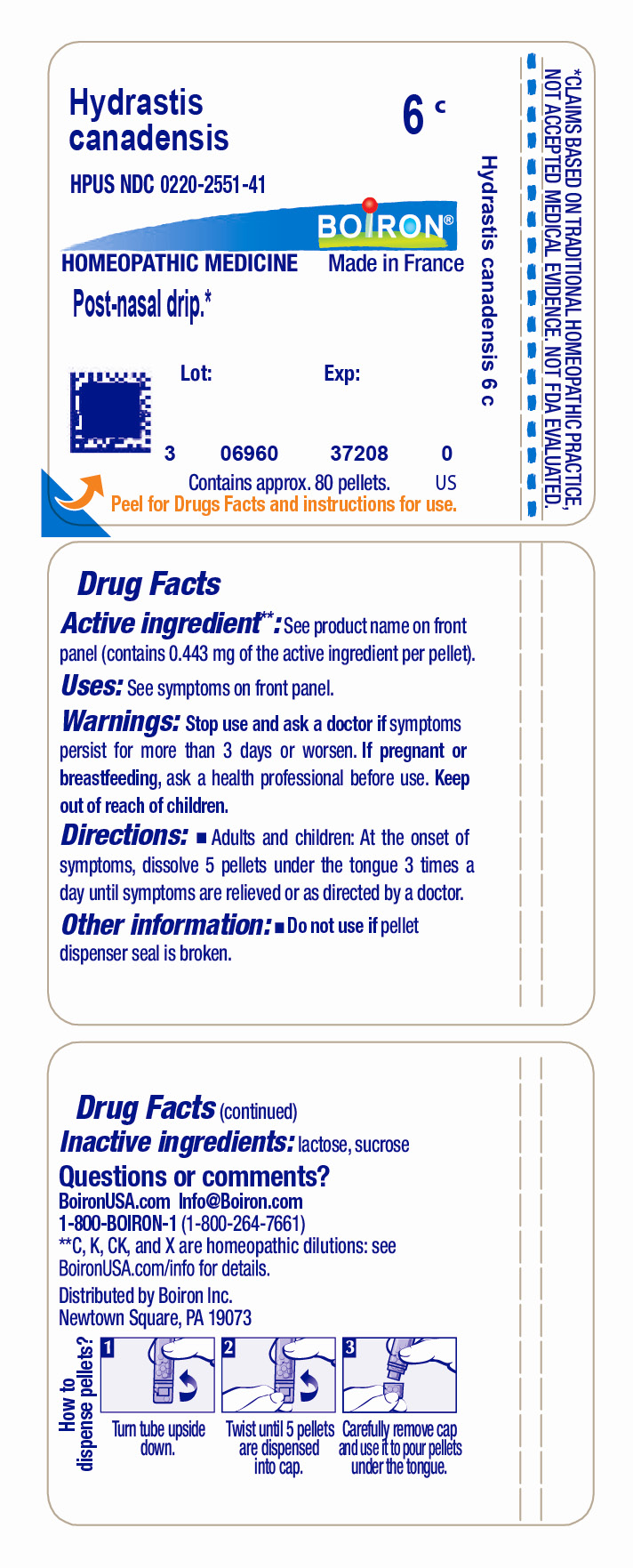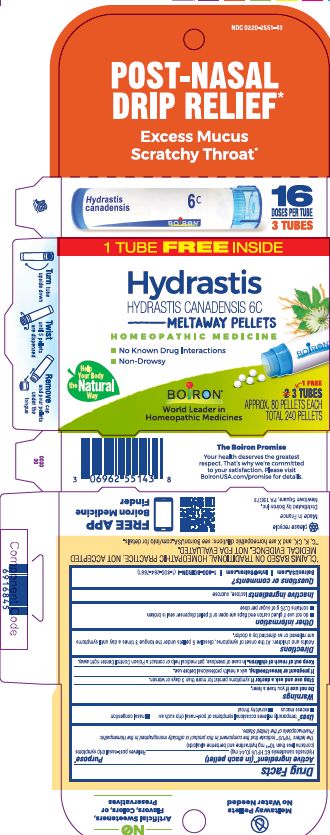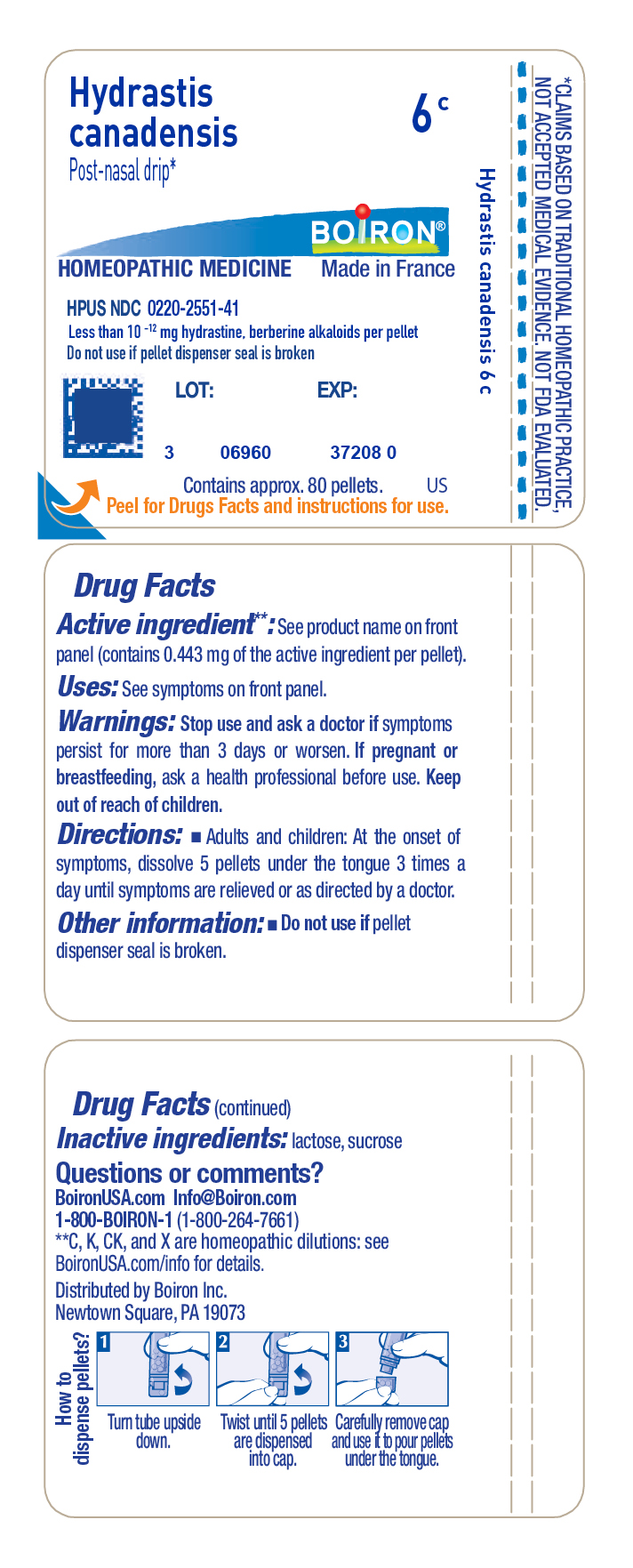 DRUG LABEL: Hydrastis candadensis
NDC: 0220-2551 | Form: PELLET
Manufacturer: Boiron
Category: homeopathic | Type: HUMAN OTC DRUG LABEL
Date: 20230120

ACTIVE INGREDIENTS: GOLDENSEAL 6 [hp_C]/6 [hp_C]
INACTIVE INGREDIENTS: SUCROSE; LACTOSE, UNSPECIFIED FORM

Hydrastis candadensis 6C

Active ingredient** (in each pellet)

Hydrastis candadensis 6C HPUS (0.44 mg)

(contains less than 10-12 mg hydrastine and berberine alkaloids)

The letter "HPUS" indicate that the component in this product is officially monographed in the Homeopathic Pharmacopoeia of the United States.

Purpose*

Hydrastis candadensis 6C HPUS (0.44 mg) ... Relieves post-nasal drip symptoms

Uses*

temporarily relieves occasional symptoms of post-nasal drip such as:

- nasal congestion
- excess mucus
- scratch throat

Tube - Post-Nasal Drip*

Do not use if you have a fever.

Stop use and ask a doctor if symptoms persist for more than 3 days or worsen

PREGNANCY OR BREAST FEEDING

If pregnant or breastfeeding, ask a health professional before use

Keep out of reach of children. In case of overdose, get medical help or contact a Poison Control Center right away.

do not use if glued carton end flaps are open or if pellet dispenser seal is broken

contains 0.25 g of sugar per dose

3 TUBES

APPROX. 80 PELLETS EACH

TOTAL 240 PELLETS

MELTAWAY PELLETS

No Known Drug Interactions

Non-Drowsy

Turn tube upside down

Twist until 5 pellets are dispensed

Remove cap and pour pellets under the tongue

Post-Nasal Drip Relief*

Excess Mucus Scratchy Throat*

Do not use if pellet dispenser seal is broken.
Contains approx. 80 pellets.
How to dispense pellets? Turn tube upside down. Twist until 5 pellets are dispensed into cap. Carefully remove the cap and use it to pour pellets under the tongue.
*CLAIMS BASED ON TRADITIONAL HOMEOPATHIC PRACTICE NOT ACCEPTED MEDICAL EVIDENCE. NOT FDA EVALUATED.
*C,K,CK, and X are homeopathic dilutions: see BoironUSA.com/info for details.

INACTIVE INGREDIENT

lactose, sucrose

DOSAGE AND ADMINISTRATION

Adults and children: At the onset of symptoms, dissolve 5 pellets under the tongue 3 times a day until symptoms are relieved or as directed by a doctor.

QUESTIONS

1-800-BOIRON-1 (1-800-264-7661),
BoironUSA.com Info@boiron.com
Distributed by Boiron, Inc. Newtown Square, PA 19073